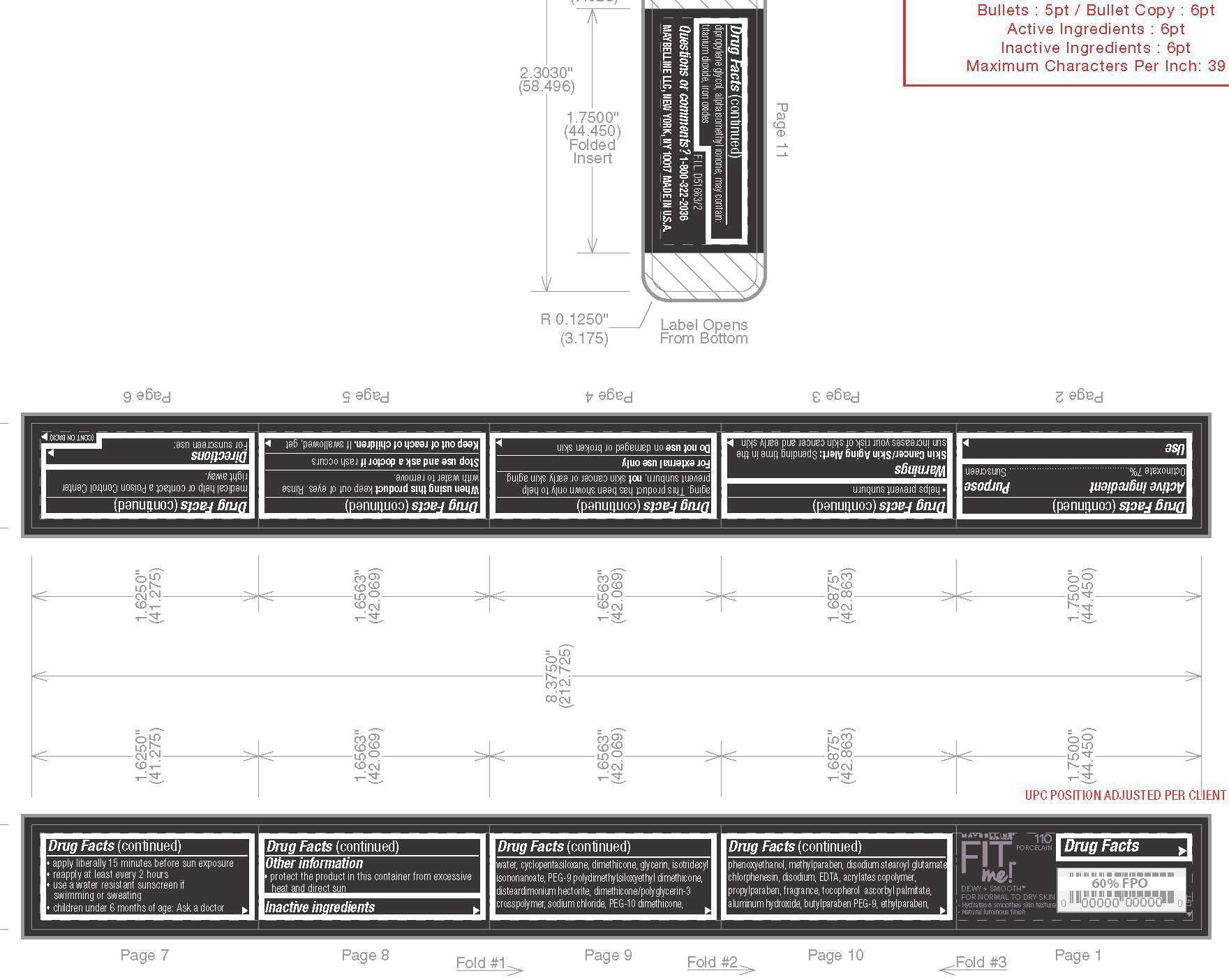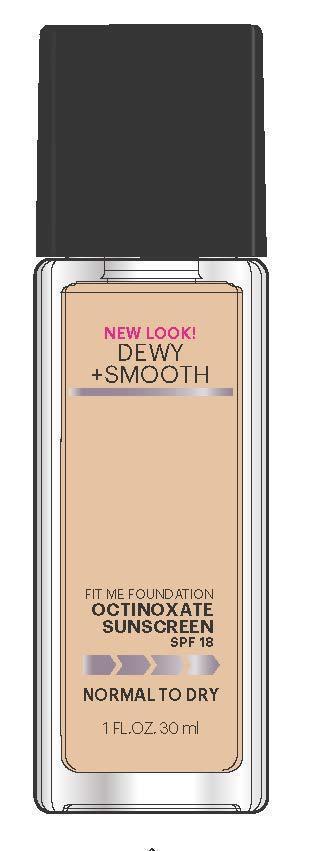 DRUG LABEL: Maybelline New York Fit Me Foundation Dewy Plus Smooth SPF 18 Sunscreen
NDC: 49967-969 | Form: LOTION
Manufacturer: L'Oreal USA Products Inc
Category: otc | Type: HUMAN OTC DRUG LABEL
Date: 20231228

ACTIVE INGREDIENTS: OCTINOXATE 70 mg/1 mL
INACTIVE INGREDIENTS: WATER; DIMETHICONE; GLYCERIN

Drug Facts

Active ingredient

Octinoxate 7%

Purpose

Sunscreen

Use

- helps prevent sunburn

Skin Cancer/Skin Aging Alert:

Spending time in the sun increases your risk of skin cancer and early skin aging. This product has been shown only to help prevent sunburn, not skin cancer or early skin aging.

Warnings

For external use only

Do not use

on damaged or broken skin

When using this product

keep out of eyes. Rinse with water to remove.

Stop use and ask a doctor if

rash occurs

Keep out of reach of children.

If swallowed, get medical help or contact a Poison Control Center right away.

Directions

For sunscreen use:

● apply liberally 15 minutes before sun exposure

● reapply at least every 2 hours

● use a water resistant sunscreen if swimming or sweating

● children under 6 months of age: Ask a doctor

Other information

- protect the product in this container from excessive heat and direct sun

Inactive ingredients

water, cyclopentasiloxane, dimethicone, glycerin, isotridecyl isononanoate, PEG-9 polydimethylsiloxyethyl dimethicone, disteardimonium hectorite, dimethicone/polyglycerin-3 crosspolymner, sodium chloride, PEG-10 dimethicone, phenoxyethanol, methylparaben, disodium stearoyl glutamate chlorphenesin, disodium, EDTA, acrylates copolymer, propylparaben, fragrance, tocopherol ascorbyl palmitate, aluminum hydroxide, butylparaben PEG-9, ethylparaben, dipropylene glycol, alphaisomethyl ionone; may contain: titanium dioxide, iron oxides